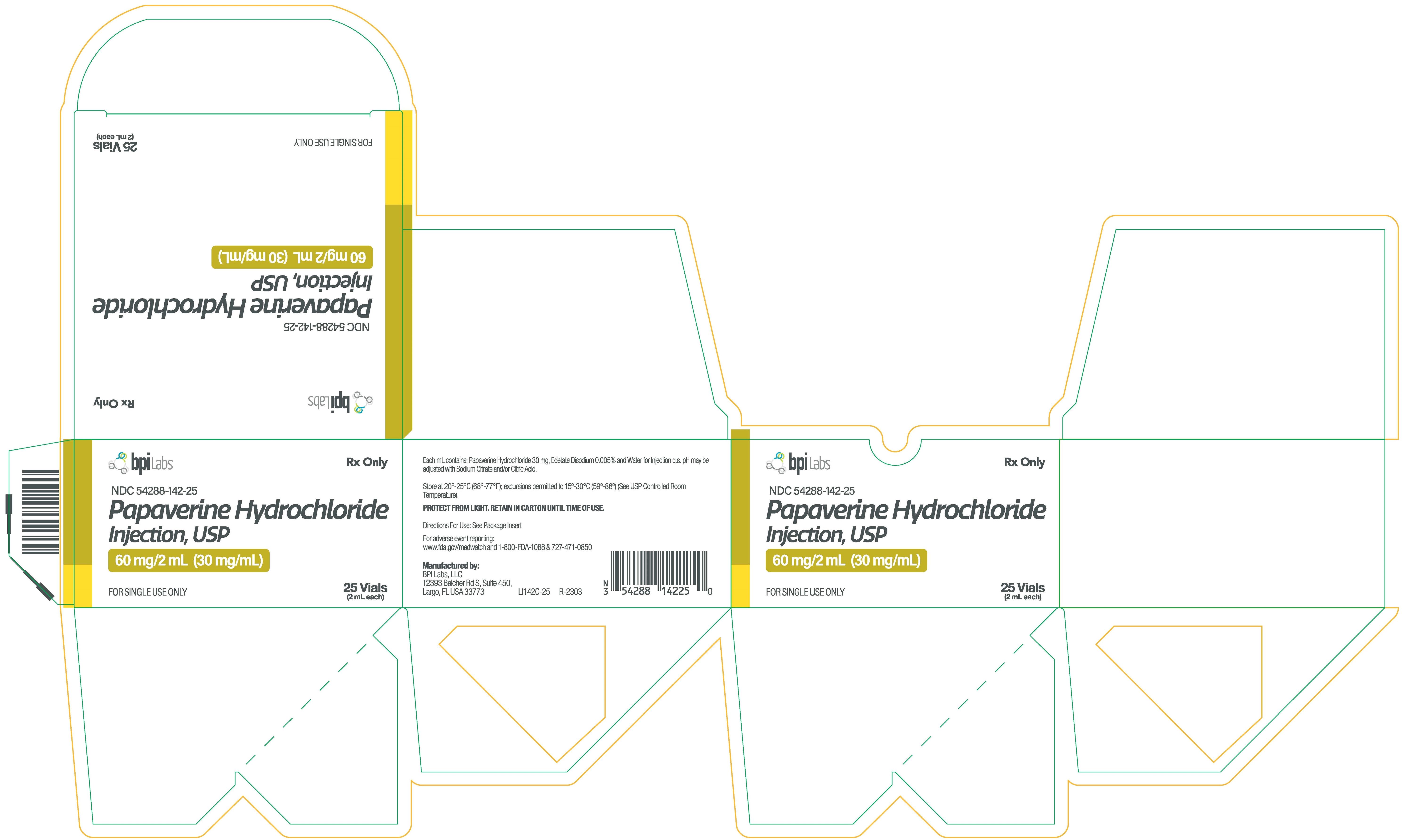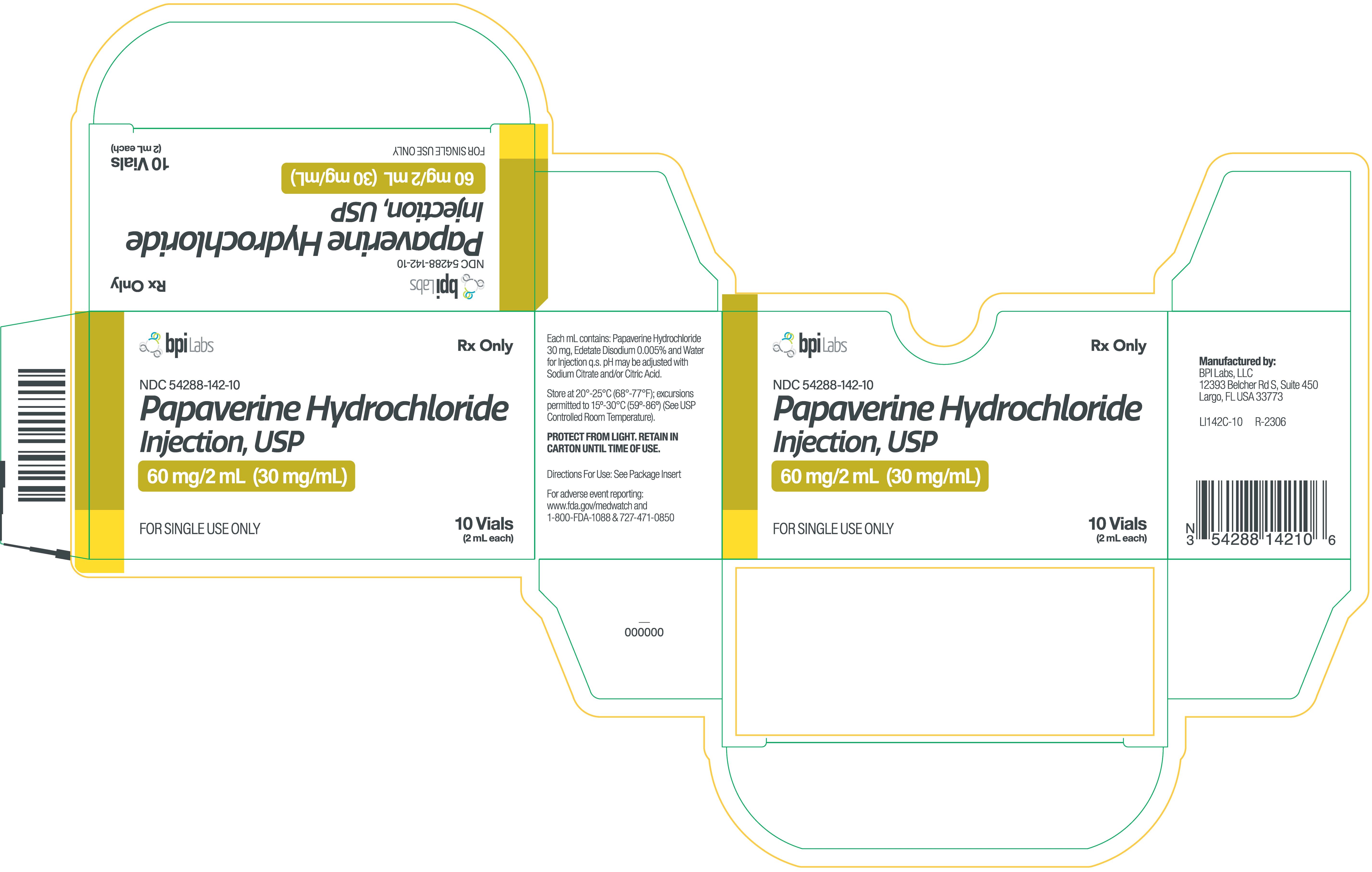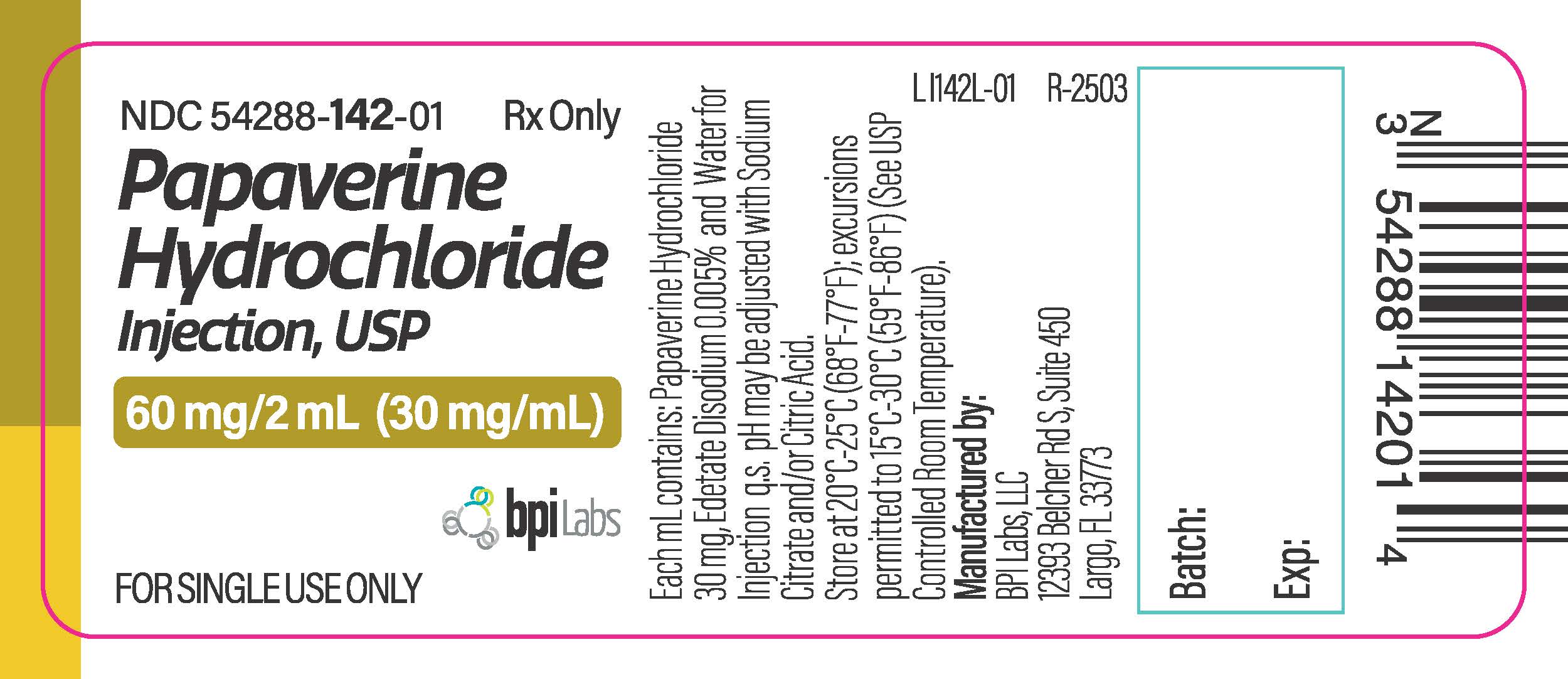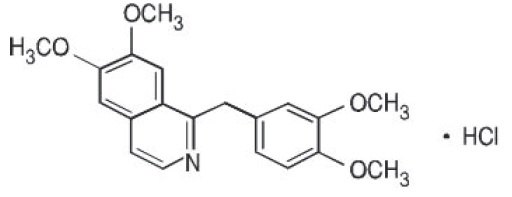 DRUG LABEL: PAPAVERINE HYDROCHLORIDE
NDC: 54288-142 | Form: INJECTION, SOLUTION
Manufacturer: BPI Labs LLC
Category: prescription | Type: HUMAN PRESCRIPTION DRUG LABEL
Date: 20251226

ACTIVE INGREDIENTS: PAPAVERINE HYDROCHLORIDE 30 mg/1 mL
INACTIVE INGREDIENTS: EDETATE DISODIUM; TRISODIUM CITRATE DIHYDRATE; CITRIC ACID MONOHYDRATE; WATER; NITROGEN

PAPAVERINE HYDROCHLORIDE INJECTION, USP
Rx Only
This product is to be used by or under the direction of a physician.
Each vial contains a sufficient amount to permit withdrawal and administration of the volume specified on the label.

DESCRIPTION

Papaverine Hydrochloride, USP, is the hydrochloride of an alkaloid obtained from opium or prepared synthetically. It belongs to the benzylisoquinoline group of alkaloids. It does not contain a phenanthrene group as do morphine and codeine.

Papaverine Hydrochloride, USP, is 6,7-dimethoxy-1- veratrylisoquinoline hydrochloride and contains, on the dried basis, not less than 98.5% of C 20H 21NO 4 •HCl. The molecular weight is 375.85. The structural formula is as shown.

Papaverine Hydrochloride occurs as white crystals or white crystalline powder. One gram dissolves in about 30 mL of water and in 120 mL of alcohol. It is soluble in chloroform and practically insoluble in ether.

Papaverine Hydrochloride Injection, USP, is a clear, colorless to pale-yellow solution.

Papaverine Hydrochloride, for parenteral administration, is a smooth-muscle relaxant that is available in vials containing 30 mg/mL. Each vial also contains edetate disodium 0.005%. pH may be adjusted with sodium citrate and/or citric acid.

CLINICAL PHARMACOLOGY

The most characteristic effect of papaverine is relaxation of the tonus of all smooth muscle, especially when it has been spasmodically contracted. Papaverine Hydrochloride apparently acts directly on the muscle itself. This relaxation is noted in the vascular system and bronchial musculature and in the gastrointestinal, biliary and urinary tracts.

The main actions of papaverine are exerted on cardiac and smooth muscle. Papaverine relaxes various smooth muscles, especially those of larger arteries; this relaxation may be prominent if spasm exists. The antispasmodic effect is a direct one and unrelated to muscle innervation, and the muscle still responds to drugs and other stimuli causing contraction. Papaverine has minimal actions on the central nervous system, although very large doses tend to produce some sedation and sleepiness in some patients. In certain circumstances, mild respiratory stimulation can be observed, but this is therapeutically inconsequential. Papaverine stimulates respiration by acting on carotid and aortic body chemoreceptors.

Papaverine relaxes the smooth musculature of the larger blood vessels, including the coronary, cerebral, peripheral, and pulmonary arteries. This action is particularly evident when such vessels are in spasm, induced reflexly or by drugs, and it provides the basis for the clinical use of papaverine in peripheral or pulmonary arterial embolism.

Experimentally in dogs, the alkaloid has been shown to cause fairly marked and long-lasting coronary vasodilatation and an increase in coronary blood flow. However, it also appears to have a direct inotropic effect and, when increased mechanical activity coincides with decreased systemic pressure, increases in coronary blood flow may not be sufficient to prevent brief periods of hypoxic myocardial depression.

Papaverine is effective by all routes of administration. A considerable fraction of the drug localizes in fat deposits and in the liver, with the remainder being distributed throughout the body. It is metabolized in the liver. About 90% of the drug is bound to plasma protein. Although estimates of its biologic half-life vary widely, reasonably constant plasma levels can be maintained with oral administration at 6 hour intervals. The drug is excreted in the urine in an inactive form.

INDICATIONS AND USAGE

Papaverine is recommended in various conditions accompanied by spasm of smooth muscle, such as vascular spasm associated with acute myocardial infarction (coronary occlusion), angina pectoris, peripheral and pulmonary embolism, peripheral vascular disease in which there is a vasospastic element, or certain cerebral angiospastic states, and visceral spasm, as in ureteral, biliary, or gastrointestinal colic.

CONTRAINDICATIONS

Intravenous injection of papaverine is contraindicated in the presence of complete atrioventricular heart block. When conduction is depressed, the drug may produce transient ectopic rhythms of ventricular origin, either premature beats or paroxysmal tachycardia.

Papaverine Hydrochloride is not indicated for the treatment of impotence by intracorporeal injection. The intracorporeal injection of papaverine hydrochloride has been reported to have resulted in persistent priapism requiring medical and surgical intervention.

PRECAUTIONS

General

Papaverine Hydrochloride Injection, USP, should not be added to Lactated Ringer's Injection, because precipitation would result.

Papaverine Hydrochloride should be used with caution in patients with glaucoma. The medication should be discontinued if hepatic hypersensitivity with gastrointestinal symptoms, jaundice, or eosinophilia becomes evident or if liver function test values become altered.

Pregnancy

Pregnancy Category C- No teratogenic effects were observed in rats when papaverine hydrochloride was administered subcutaneously as a single agent. It is not known whether papaverine can cause fetal harm when administered to a pregnant woman or can affect reproduction capacity. Papaverine Hydrochloride should be given to a pregnant woman only if clearly needed.

Nursing Mothers

It is not known whether this drug is excreted in human milk. Because many drugs are excreted in human milk, caution should be exercised when papaverine hydrochloride is administered to a nursing woman.

Pediatric Use

Safety and effectiveness in children have not been established.

ADVERSE REACTIONS

The following side effects have been reported: general discomfort, nausea, abdominal discomfort, anorexia, constipation or diarrhea, skin rash, malaise, vertigo, headache, intensive flushing of the face, perspiration, increase in the depth of respiration, increase in heart rate, a slight rise in blood pressure, and excessive sedation.

Hepatitis, probably related to an immune mechanism, has been reported infrequently. Rarely, this has progressed to cirrhosis.

To report SUSPECTED ADVERSE REACTIONS, contact BPI Labs, LLC at (727) 471-0850 or FDA at 1-800-FDA-1088 or www.fda.gov/medwatch

DRUG ABUSE AND DEPENDENCE

Drug dependence resulting from the abuse of many of the selective depressants, including papaverine hydrochloride, has been reported.

OVERDOSAGE

Signs and Symptoms -

The symptoms of toxicity from papaverine hydrochloride often result from vasomotor instability and include nausea, vomiting, weakness, central nervous system depression, nystagmus, diplopia, diaphoresis, flushing, dizziness, and sinus tachycardia. In large overdoses, papaverine is a potent inhibitor of cellular respiration and a weak calcium antagonist. Following an oral overdose of 15 g, metabolic acidosis with hyperventilation, hyperglycemia, and hypokalemia have been reported. No information on toxic serum concentrations is available.

Following intravenous overdosing in animals, seizures, tachyarrhythmias, and ventricular fibrillation have been reported. The oral median lethal dose in rats is 360 mg/kg.

Treatment-

To obtain up-to-date information about the treatment of overdose, a good resource is your certified Regional Poison Control Center. Telephone numbers of certified poison control centers are listed in the Physician’s Desk Reference (PDR) In managing overdosage, consider the possibility of multiple drug overdoses, interaction among drugs, and unusual drug kinetics in your patient.

Protect the patient's airway and support ventilation and perfusion. Meticulously monitor vital signs, blood gases, blood chemistry values, and other variables.

If convulsions occur, consider diazepam, phenytoin, or phenobarbital. If the seizures are refractory, general anesthesia with thiopental or halothane and paralysis with a neuromuscular blocking agent may be necessary.

For hypotension, consider intravenous fluids, elevation of the legs, and an inotropic vasopressor, such as dopamine or norepinephrine (levarterenol). Theoretically, calcium gluconate may be helpful in treating some of the toxic cardiovascular effects of papaverine; monitor the ECG and plasma calcium concentrations.

Forced diuresis, peritoneal dialysis, hemodialysis, or charcoal hemoperfusion have not been established as beneficial for an overdose of papaverine hydrochloride.

DOSAGE AND ADMINISTRATION

Papaverine Hydrochloride may be administered intravenously or intramuscularly. The intravenous route is recommended when an immediate effect is desired, but the drug must be injected slowly over the course of 1 or 2 minutes to avoid uncomfortable or alarming side effects.

Parenteral administration of papaverine hydrochloride in doses of 1 to 4 mL is repeated every 3 hours as indicated. In the treatment of cardiac extrasystoles, 2 doses may be given 10 minutes apart.

HOW SUPPLIED

Papaverine Hydrochloride Injection, USP, 30 mg/mL is available as

54288-142-10 2mL Vial packaged in boxes of 10.

54288-142-25 2mL Vial packaged in boxes of 25.

Store at 20° to 25°C (68° to 77°F); excursions permitted to 15° to 30°C (59° to 86°F) (See USP Controlled Room Temperature).
PROTECT FROM LIGHT. RETAIN IN CARTON UNTIL TIME OF USE.

Manufactured by:

BPI Labs, LLC

12393 Belcher Rd S, Suite 450

Largo, FL USA 33773

LI33I

R-2303